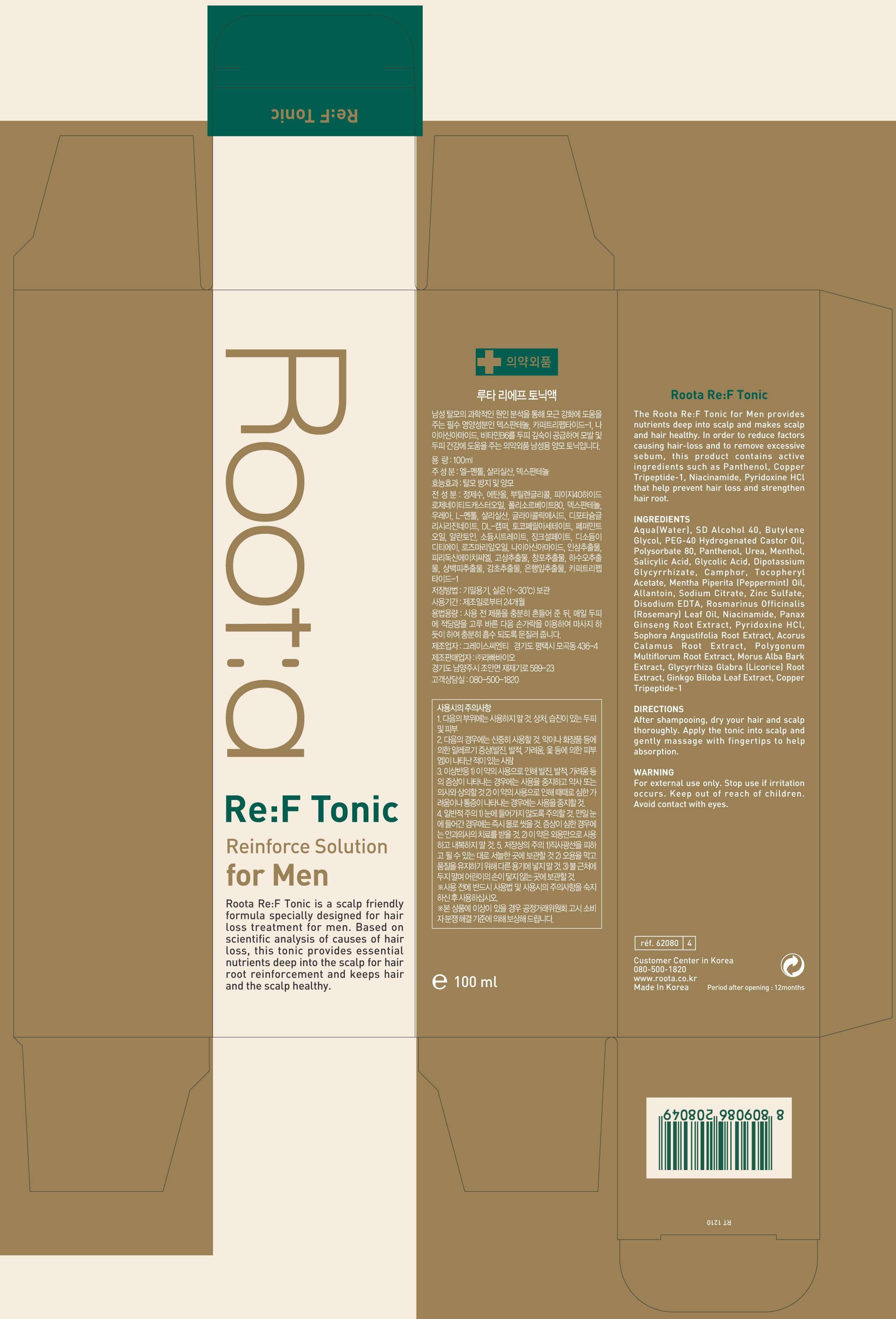 DRUG LABEL: Roota Re F Tonic
                
NDC: 54576-3001 | Form: LIQUID
Manufacturer: Raphabio Inc
Category: otc | Type: HUMAN OTC DRUG LABEL
Date: 20121231

ACTIVE INGREDIENTS: PANTHENOL 0.5 mg/100 mL
INACTIVE INGREDIENTS: WATER; ALCOHOL; BUTYLENE GLYCOL; POLYOXYL 40 HYDROGENATED CASTOR OIL; POLYSORBATE 80; UREA; MENTHOL; SALICYLIC ACID; GLYCOLIC ACID; GLYCYRRHIZINATE DIPOTASSIUM; CAMPHOR (NATURAL); .ALPHA.-TOCOPHEROL ACETATE; MENTHA PIPERITA; ALLANTOIN; SODIUM CITRATE; ZINC SULFATE; EDETATE DISODIUM; ROSEMARY; NIACINAMIDE; ASIAN GINSENG; PYRIDOXINE HYDROCHLORIDE; SOPHORA FLAVESCENS ROOT; ACORUS CALAMUS ROOT; FALLOPIA MULTIFLORA ROOT; MORUS ALBA BARK; GLYCYRRHIZA GLABRA; GINKGO; PREZATIDE COPPER

Drug Facts

ACTIVE INGREDIENT

panthenol

INACTIVE INGREDIENT

Aqua (Water), sd alcohol 40, butylene glycol, peg-40 hydrogenated castor oil, polysorbate 80, urea, menthol, salicylic acid, glycolic acid, dipotassium glycyrrhizate, camphor, tocopheryl acetate, peppermint oil, allantoin, sodium citrate, zinc sulfate, disodium edta, rosemary leaf oil, niacinamide, panax ginseng root extract, pyridoxine hci, sophora angustifolia root extract, acorus calamus root extract, polygonum multiflorum root extract, morus alba bark extract, licorice root extract, ginkgo biloba leaf extract, copper tripeptide-1

PURPOSE

hair care

keep out of reach of the children

INDICATIONS AND USAGE

after shampooing, dry your hair and sclap thoroughly
apply the tonic into scalp and gently massage with fingertips to help absorption

stop use if irritation occurs

DOSAGE AND ADMINISTRATION

for external use only